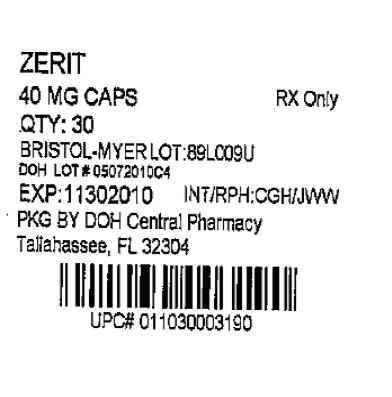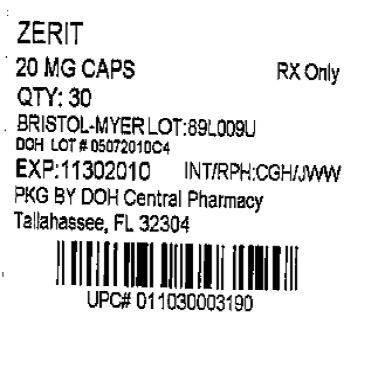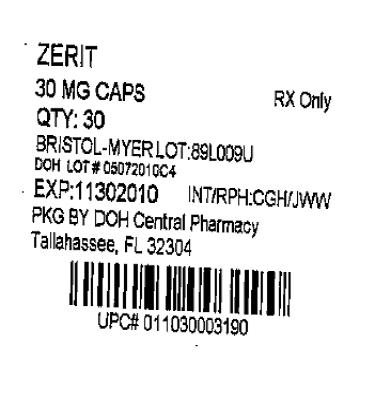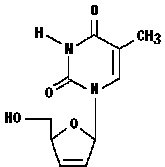 DRUG LABEL: ZERIT
NDC: 53808-0656 | Form: CAPSULE, GELATIN COATED
Manufacturer: State of Florida DOH Central Pharmacy
Category: prescription | Type: HUMAN PRESCRIPTION DRUG LABEL
Date: 20100812

ACTIVE INGREDIENTS: STAVUDINE 20 mg/1 1
INACTIVE INGREDIENTS: CELLULOSE, MICROCRYSTALLINE; SODIUM STARCH GLYCOLATE TYPE A POTATO; LACTOSE; MAGNESIUM STEARATE; GELATIN; TITANIUM DIOXIDE

ZERIT® (stavudine) Capsules
ZERIT® (stavudine) for Oral Solution

(Patient Information Leaflet Included)

WARNING

LACTIC ACIDOSIS AND SEVERE HEPATOMEGALY WITH STEATOSIS, INCLUDING FATAL CASES, HAVE BEEN REPORTED WITH THE USE OF NUCLEOSIDE ANALOGUES ALONE OR IN COMBINATION, INCLUDING STAVUDINE AND OTHER ANTIRETROVIRALS. FATAL LACTIC ACIDOSIS HAS BEEN REPORTED IN PREGNANT WOMEN WHO RECEIVED THE COMBINATION OF STAVUDINE AND DIDANOSINE WITH OTHER ANTIRETROVIRAL AGENTS. THE COMBINATION OF STAVUDINE AND DIDANOSINE SHOULD BE USED WITH CAUTION DURING PREGNANCY AND IS RECOMMENDED ONLY IF THE POTENTIAL BENEFIT CLEARLY OUTWEIGHS THE POTENTIAL RISK (SEE WARNINGS AND PRECAUTIONS: PREGNANCY).

FATAL AND NONFATAL PANCREATITIS HAVE OCCURRED DURING THERAPY WHEN ZERIT WAS PART OF A COMBINATION REGIMEN THAT INCLUDED DIDANOSINE IN BOTH TREATMENT-NAIVE AND TREATMENT-EXPERIENCED PATIENTS, REGARDLESS OF DEGREE OF IMMUNOSUPPRESSION (SEE WARNINGS).

DESCRIPTION

ZERIT® is the brand name for stavudine (d4T), a synthetic thymidine nucleoside analogue, active against the human immunodeficiency virus (HIV).

ZERIT (stavudine) Capsules are supplied for oral administration in strengths of 15, 20, 30, and 40 mg of stavudine. Each capsule also contains inactive ingredients microcrystalline cellulose, sodium starch glycolate, lactose, and magnesium stearate. The hard gelatin shell consists of gelatin, titanium dioxide, and iron oxides. The capsules are printed with edible inks.

ZERIT (stavudine) for Oral Solution is supplied as a dye-free, fruit-flavored powder in bottles with child-resistant closures providing 200 mL of a 1 mg/mL stavudine solution upon constitution with water per label instructions. The powder for oral solution contains the following inactive ingredients: methylparaben, propylparaben, sodium carboxymethylcellulose, sucrose, and antifoaming and flavoring agents.

The chemical name for stavudine is 2',3'-didehydro-3'-deoxythymidine. Stavudine has the following structural formula:

Stavudine is a white to off-white crystalline solid with the molecular formula C10H12N2O4 and a molecular weight of 224.2. The solubility of stavudine at 23° C is approximately 83 mg/mL in water and 30 mg/mL in propylene glycol. The n-octanol/water partition coefficient of stavudine at 23° C is 0.144.

MICROBIOLOGY

Mechanism of Action

Stavudine, a nucleoside analogue of thymidine, is phosphorylated by cellular kinases to the active metabolite stavudine triphosphate. Stavudine triphosphate inhibits the activity of HIV-1 reverse transcriptase (RT) by competing with the natural substrate thymidine triphosphate (Ki=0.0083 to 0.032 µM) and by causing DNA chain termination following its incorporation into viral DNA. Stavudine triphosphate inhibits cellular DNA polymerases β and γ and markedly reduces the synthesis of mitochondrial DNA.

Antiviral Activity

The cell culture antiviral activity of stavudine was measured in peripheral blood mononuclear cells, monocytic cells, and lymphoblastoid cell lines. The concentration of drug necessary to inhibit HIV-1 replication by 50% (EC50) ranged from 0.009 to 4 µM against laboratory and clinical isolates of HIV-1. In cell culture, stavudine exhibited additive to antagonistic activity in combination with zidovudine. Stavudine in combination with either abacavir, didanosine, tenofovir, or zalcitabine exhibited additive to synergistic anti-HIV-1 activity. Ribavirin, at the 9‑45 µM concentrations tested, reduced the anti-HIV-1 activity of stavudine by 2.5- to 5-fold. The relationship between cell culture susceptibility of HIV-1 to stavudine and the inhibition of HIV-1 replication in humans has not been established.

Drug Resistance

HIV-1 isolates with reduced susceptibility to stavudine have been selected in cell culture (strain-specific) and were also obtained from patients treated with stavudine. Phenotypic analysis of HIV-1 isolates from 61 patients receiving prolonged (6-29 months) stavudine monotherapy showed that post-therapy isolates from four patients exhibited EC50 values more than 4-fold (range 7- to 16-fold) higher than the average pretreatment susceptibility of baseline isolates. Of these, HIV-1 isolates from one patient contained the zidovudine-resistance-associated mutations T215Y and K219E, and isolates from another patient contained the multiple-nucleoside-resistance-associated mutation Q151M. Mutations in the RT gene of HIV-1 isolates from the other two patients were not detected. The genetic basis for stavudine susceptibility changes has not been identified.

Cross-resistance

Cross-resistance among HIV-1 reverse transcriptase inhibitors has been observed. Several studies have demonstrated that prolonged stavudine treatment can select and/or maintain mutations associated with zidovudine resistance. HIV-1 isolates with one or more zidovudine-resistance-associated mutations (M41L, D67N, K70R, L210W, T215Y/F, K219Q/E) exhibited reduced susceptibility to stavudine in cell culture.

CLINICAL PHARMACOLOGY

Pharmacokinetics

The pharmacokinetics of stavudine have been evaluated in HIV-infected adult and pediatric patients (Tables 1-3). Peak plasma concentrations (Cmax) and area under the plasma concentration-time curve (AUC) increased in proportion to dose after both single and multiple doses ranging from 0.03 to 4 mg/kg. There was no significant accumulation of stavudine with repeated administration every 6, 8, or 12 hours.

Absorption

Following oral administration, stavudine is rapidly absorbed, with peak plasma concentrations occurring within 1 hour after dosing. The systemic exposure to stavudine is the same following administration as capsules or solution. Steady-state pharmacokinetic parameters of ZERIT (stavudine) in HIV-infected adults are shown in Table 1.

Table 1: Steady-State Pharmacokinetic Parameters of ZERIT in HIV-Infected Adults
Parameter | ZERIT 40 mg BID Mean ± SD (n=8)
AUC (ng•h/mL)a | 2568 ± 454
Cmax (ng/mL) | 536 ± 146
Cmin (ng/mL) | 8 ± 9
a from 0 to 24 hours.
AUC = area under the curve over 24 hours.
Cmax = maximum plasma concentration.
Cmin = trough or minimum plasma concentration.

Distribution

Binding of stavudine to serum proteins was negligible over the concentration range of 0.01 to 11.4 µg/mL. Stavudine distributes equally between red blood cells and plasma. Volume of distribution is shown in Table 2.

Metabolism

Metabolism plays a limited role in the clearance of stavudine. Unchanged stavudine was the major drug-related component circulating in plasma after an 80-mg dose of ^14C-stavudine, while metabolites constituted minor components of the circulating radioactivity. Minor metabolites include oxidized stavudine, glucuronide conjugates of stavudine and its oxidized metabolite, and an N-acetylcysteine conjugate of the ribose after glycosidic cleavage, suggesting that thymine is also a metabolite of stavudine.

Elimination

Following an 80-mg dose of ^14C-stavudine to healthy subjects, approximately 95% and 3% of the total radioactivity was recovered in urine and feces, respectively. Radioactivity due to parent drug in urine and feces was 73.7% and 62.0%, respectively. The mean terminal elimination half-life is approximately 2.3 hours following single oral doses. Mean renal clearance of the parent compound is approximately 272 mL/min, accounting for approximately 67% of the apparent oral clearance.

In HIV-infected patients, renal elimination of unchanged drug accounts for about 40% of the overall clearance regardless of the route of administration (Table 2). The mean renal clearance was about twice the average endogenous creatinine clearance, indicating active tubular secretion in addition to glomerular filtration.

Table 2: Pharmacokinetic Parameters of Stavudine in HIV-Infected Adults: Bioavailability, Distribution, and Clearance
Parameter | Mean ± SD | n
Oral bioavailability (%) | 86.4 ± 18.2 | 25
Volume of distribution (L)a | 46 ± 21 | 44
Total body clearance (mL/min)a | 594 ± 164 | 44
Apparent oral clearance (mL/min)b | 560 ± 182c | 113
Renal clearance (mL/min)a | 237 ± 98 | 39
Elimination half-life, IV dose (h)a | 1.15 ± 0.35 | 44
Elimination half-life, oral dose (h)b | 1.6 ± 0.23 | 8
Urinary recovery of stavudine (% of dose)a,d | 42 ± 14 | 39
a following 1-hour IV infusion.
b following single oral dose.
c assuming a body weight of 70 kg.
d over 12-24 hours.

Pediatric

For pharmacokinetic properties of stavudine in pediatric patients see Table 3.

Table 3: Pharmacokinetic Parameters (Mean ± SD) of Stavudine in HIV-Exposed or -Infected Pediatric Patients
Parameter | Ages 5 weeks to 15 years | n | Ages 14 to 28 days | n | Day of Birth | n
Oral bioavailability (%) | 76.9 ± 31.7 | 20 | ND |  | ND
Volume of distribution (L/kg)a | 0.73 ± 0.32 | 21 | ND |  | ND
Ratio of CSF: plasma concentrations (as %)b | 59 ± 35 | 8 | ND |  | ND
Total body clearance (mL/min/kg)a | 9.75 ± 3.76 | 21 | ND |  | ND
Apparent oral clearance (mL/min/kg)c | 13.75 ± 4.29 | 20 | 11.52 ± 5.93 | 30 | 5.08 ± 2.80 | 17
Elimination half-life, IV dose (h)a | 1.11 ± 0.28 | 21 | ND |  | ND
Elimination half-life, oral dose (h)c | 0.96 ± 0.26 | 20 | 1.59 ± 0.29 | 30 | 5.27 ± 2.01 | 17
Urinary recovery of stavudine (% of dose)c,d | 34 ± 16 | 19 | ND |  | ND
a following 1-hour IV infusion.
b at median time of 2.5 hours (range 2-3 hours) following multiple oral doses.
c following single oral dose.
d over 8 hours.
ND = not determined.

Renal Impairment

Data from two studies in adults indicated that the apparent oral clearance of stavudine decreased and the terminal elimination half-life increased as creatinine clearance decreased (see Table 4). Cmax and Tmax were not significantly altered by renal impairment. The mean ± SD hemodialysis clearance value of stavudine was 120 ± 18 mL/min (n=12); the mean ± SD percentage of the stavudine dose recovered in the dialysate, timed to occur between 2-6 hours post-dose, was 31 ± 5%. Based on these observations, it is recommended that ZERIT (stavudine) dosage be modified in patients with reduced creatinine clearance and in patients receiving maintenance hemodialysis (see DOSAGE AND ADMINISTRATION).

Table 4: Mean ± SD Pharmacokinetic Parameter Values of ZERITa in Adults with Varying Degrees of Renal Function
 | Creatinine Clearance |  |  | Hemodialysis Patientsb (n=11)
 | >50 mL/min (n=10) | 26-50 mL/min (n=5) | 9-25 mL/min (n=5) | Hemodialysis Patientsb (n=11)
Creatinine clearance (mL/min) | 104 ± 28 | 41 ± 5 | 17 ± 3 | NA
Apparent oral clearance (mL/min) | 335 ± 57 | 191 ± 39 | 116 ± 25 | 105 ± 17
Renal clearance (mL/min) | 167 ± 65 | 73 ± 18 | 17 ± 3 | NA
T½ (h) | 1.7 ± 0.4 | 3.5 ± 2.5 | 4.6 ± 0.9 | 5.4 ± 1.4
a Single 40-mg oral dose.
b Determined while patients were off dialysis.
T½ = terminal elimination half-life.
NA = not applicable.

Hepatic Impairment

Stavudine pharmacokinetics were not altered in five non-HIV-infected patients with hepatic impairment secondary to cirrhosis (Child-Pugh classification B or C) following the administration of a single 40-mg dose.

Geriatric

Stavudine pharmacokinetics have not been studied in patients >65 years of age. (See PRECAUTIONS: Geriatric Use.)

Gender

A population pharmacokinetic analysis of data collected during a controlled clinical study in HIV-infected patients showed no clinically important differences between males (n=291) and females (n=27).

Race

A population pharmacokinetic analysis of data collected during a controlled clinical study in HIV-infected patients showed no clinically important differences between races (n=233 Caucasian, 39 African-American, 41 Hispanic, 1 Asian, and 4 other).

Drug Interactions (see PRECAUTIONS: Drug Interactions)

Zidovudine: Zidovudine competitively inhibits the intracellular phosphorylation of stavudine. Therefore, use of zidovudine in combination with ZERIT (stavudine) should be avoided.

Doxorubicin: In vitro data indicate that the phosphorylation of stavudine is inhibited at relevant concentrations by doxorubicin.

Ribavirin: In vitro data indicate ribavirin reduces phosphorylation of lamivudine, stavudine, and zidovudine. However, no pharmacokinetic (eg, plasma concentrations or intracellular triphosphorylated active metabolite concentrations) or pharmacodynamic (eg, loss of HIV/HCV virologic suppression) interaction was observed when ribavirin and lamivudine (n=18), stavudine (n=10), or zidovudine (n=6) were coadministered as part of a multi-drug regimen to HIV/HCV co-infected patients (see WARNINGS).

Stavudine does not inhibit the major cytochrome P450 isoforms CYP1A2, CYP2C9, CYP2C19, CYP2D6, and CYP3A4; therefore, it is unlikely that clinically significant drug interactions will occur with drugs metabolized through these pathways.

Because stavudine is not protein-bound, it is not expected to affect the pharmacokinetics of protein-bound drugs.

Tables 5 and 6 summarize the effects on AUC and Cmax, with a 95% confidence interval (CI) when available, following coadministration of ZERIT with didanosine, lamivudine, and nelfinavir. No clinically significant pharmacokinetic interactions were observed.

Table 5: Results of Drug Interaction Studies with ZERIT: Effects of Coadministered Drug on Stavudine Plasma AUC and Cmax Values
Drug | Stavudine Dosage | na | AUC of Stavudine (95% CI) | Cmax of Stavudine (95% CI)
Didanosine, 100 mg q12h for 4 days | 40 mg q12h for 4 days | 10 | ↔ | ↑ 17%
Lamivudine, 150 mg single dose | 40 mg single dose | 18 | ↔ (92.7-100.6%) | ↑12% (100.3-126.1%)
Nelfinavir, 750 mg q8h for 56 days | 30-40 mg q12h for 56 days | 8 | ↔ | ↔
↑ indicates increase.
↔ indicates no change, or mean increase or decrease of <10%.
a HIV-infected patients.

Table 6: Results of Drug Interaction Studies with ZERIT: Effects of Stavudine on Coadministered Drug Plasma AUC and Cmax Values
Drug | Stavudine Dosage | na | AUC of Coadministered Drug (95% CI) | Cmax of Coadministered Drug (95% CI)
Didanosine, 100 mg q12h for 4 days | 40 mg q12h for 4 days | 10 | ↔ | ↔
Lamivudine, 150 mg single dose | 40 mg single dose | 18 | ↔ (90.5-107.6%) | ↔ (87.1-110.6%)
Nelfinavir, 750 mg q8h for 56 days | 30-40 mg q12h for 56 days | 8 | ↔ | ↔
↔ indicates no change, or mean increase or decrease of <10%.
a HIV-infected patients.

INDICATIONS AND USAGE

ZERIT (stavudine), in combination with other antiretroviral agents, is indicated for the treatment of HIV-1 infection (see Clinical Studies).

Combination Therapy

The combination use of ZERIT is based on the results of clinical studies in HIV-infected patients in double- and triple-combination regimens with other antiretroviral agents.

One of these studies (START 1) was a multicenter, randomized, open-label study comparing ZERIT (40 mg twice daily) plus lamivudine plus indinavir to zidovudine plus lamivudine plus indinavir in 202 treatment-naive patients. Both regimens resulted in a similar magnitude of inhibition of HIV RNA levels and increases in CD4 cell counts through 48 weeks.

Monotherapy

The efficacy of ZERIT was demonstrated in a randomized, double-blind study (AI455-019, conducted 1992-1994) comparing ZERIT with zidovudine in 822 patients with a spectrum of HIV-related symptoms. The outcome in terms of progression of HIV disease and death was similar for both drugs.

CONTRAINDICATIONS

ZERIT is contraindicated in patients with clinically significant hypersensitivity to stavudine or to any of the components contained in the formulation.

WARNINGS

1. Lactic Acidosis/Severe Hepatomegaly with Steatosis:

Lactic acidosis and severe hepatomegaly with steatosis, including fatal cases, have been reported with the use of nucleoside analogues alone or in combination, including stavudine and other antiretrovirals. Although relative rates of lactic acidosis have not been assessed in prospective well-controlled trials, longitudinal cohort and retrospective studies suggest that this infrequent event may be more often associated with antiretroviral combinations containing stavudine. Female gender, obesity, and prolonged nucleoside exposure may be risk factors. Fatal lactic acidosis has been reported in pregnant women who received the combination of stavudine and didanosine with other antiretroviral agents. The combination of stavudine and didanosine should be used with caution during pregnancy and is recommended only if the potential benefit clearly outweighs the potential risk (see PRECAUTIONS: Pregnancy).

Particular caution should be exercised when administering ZERIT to any patient with known risk factors for liver disease; however, cases of lactic acidosis have also been reported in patients with no known risk factors. Generalized fatigue, digestive symptoms (nausea, vomiting, abdominal pain, and unexplained weight loss); respiratory symptoms (tachypnea and dyspnea); or neurologic symptoms (including motor weakness, see 3. Neurologic Symptoms) might be indicative of the development of symptomatic hyperlactatemia or lactic acidosis syndrome.

Treatment with ZERIT (stavudine) should be suspended in any patient who develops clinical or laboratory findings suggestive of symptomatic hyperlactatemia, lactic acidosis, or pronounced hepatotoxicity (which may include hepatomegaly and steatosis even in the absence of marked transaminase elevations).

2. Hepatic Impairment and Toxicity:

The safety and efficacy of ZERIT have not been established in HIV-infected patients with significant underlying liver disease. During combination antiretroviral therapy, patients with preexisting liver dysfunction, including chronic active hepatitis, have an increased frequency of liver function abnormalities, including severe and potentially fatal hepatic adverse events, and should be monitored according to standard practice. If there is evidence of worsening liver disease in such patients, interruption or discontinuation of treatment must be considered.

An increased risk of hepatotoxicity may occur in patients treated with ZERIT in combination with didanosine and hydroxyurea compared to when ZERIT is used alone. Deaths attributed to hepatotoxicity have occurred in patients receiving this combination. This combination should be avoided.

Use with Interferon and Ribavirin-Based Regimens

In vitro studies have shown ribavirin can reduce the phosphorylation of pyrimidine nucleoside analogues such as stavudine. Although no evidence of a pharmacokinetic or pharmacodynamic (eg, loss of HIV/HCV virologic suppression) interaction was seen when ribavirin was coadministered with stavudine in HIV/HCV co-infected patients (see CLINICAL PHARMACOLOGY: Drug Interactions), hepatic decompensation (some fatal) has occurred in HIV/HCV co-infected patients receiving combination antiretroviral therapy for HIV and interferon and ribavirin. Patients receiving interferon with or without ribavirin and stavudine should be closely monitored for treatment-associated toxicities, especially hepatic decompensation. Discontinuation of stavudine should be considered as medically appropriate. Dose reduction or discontinuation of interferon, ribavirin, or both should also be considered if worsening clinical toxicities are observed, including hepatic decompensation (eg, Child-Pugh >6) (see the complete prescribing information for interferon and ribavirin).

3. Neurologic Symptoms:

Motor weakness has been reported rarely in patients receiving combination antiretroviral therapy including ZERIT. Most of these cases occurred in the setting of lactic acidosis. The evolution of motor weakness may mimic the clinical presentation of Guillain-Barré syndrome (including respiratory failure). Symptoms may continue or worsen following discontinuation of therapy.

Peripheral neuropathy, manifested by numbness, tingling, or pain in the hands or feet, has been reported in patients receiving ZERIT therapy. Peripheral neuropathy has occurred more frequently in patients with advanced HIV disease, with a history of neuropathy, or in patients receiving other drugs that have been associated with neuropathy, including didanosine (see ADVERSE REACTIONS).

4. Pancreatitis:

Fatal and nonfatal pancreatitis have occurred during therapy when ZERIT was part of a combination regimen that included didanosine in both treatment-naive and treatment-experienced patients, regardless of degree of immunosuppression. The combination of ZERIT and didanosine and any other agents that are toxic to the pancreas should be suspended in patients with suspected pancreatitis. Reinstitution of ZERIT after a confirmed diagnosis of pancreatitis should be undertaken with particular caution and close patient monitoring. The new regimen should not contain didanosine.

PRECAUTIONS

Fat Redistribution

Redistribution/accumulation of body fat including central obesity, dorsocervical fat enlargement (buffalo hump), peripheral wasting, facial wasting, breast enlargement, and “cushingoid appearance” have been observed in patients receiving antiretroviral therapy. The mechanism and long-term consequences of these events are currently unknown. A causal relationship has not been established.

Immune reconstitution syndrome has been reported in patients treated with combination antiretroviral therapy, including ZERIT. During the initial phase of combination antiretroviral treatment, patients whose immune system responds may develop an inflammatory response to indolent or residual opportunistic infections (such as Mycobacterium avium infection, cytomegalovirus, Pneumocystis jiroveci pneumonia (PCP), or tuberculosis), which may necessitate further evaluation and treatment.

Information for Patients (See Patient Information Leaflet.)

Patients should be informed of the importance of early recognition of symptoms of symptomatic hyperlactatemia or lactic acidosis syndrome, which include unexplained weight loss, abdominal discomfort, nausea, vomiting, fatigue, dyspnea, and motor weakness. Patients in whom these symptoms develop should seek medical attention immediately. Discontinuation of ZERIT therapy may be required.

Patients should be informed that an important toxicity of ZERIT (stavudine) is peripheral neuropathy. Patients should be aware that peripheral neuropathy is manifested by numbness, tingling, or pain in hands or feet, and that these symptoms should be reported to their physicians. Patients should be counseled that peripheral neuropathy occurs with greatest frequency in patients who have advanced HIV disease or a history of peripheral neuropathy, and that dose modification and/or discontinuation of ZERIT may be required if toxicity develops.

Caregivers of young children receiving ZERIT therapy should be instructed regarding detection and reporting of peripheral neuropathy.

Patients should be informed that when ZERIT is used in combination with other agents with similar toxicities, the incidence of adverse events may be higher than when ZERIT is used alone. An increased risk of pancreatitis, which may be fatal, may occur in patients treated with the combination of ZERIT and didanosine. Patients treated with this combination should be closely monitored for symptoms of pancreatitis. An increased risk of hepatotoxicity, which may be fatal, may occur in patients treated with ZERIT in combination with didanosine and hydroxyurea. This combination should be avoided.

Patients should be informed that ZERIT (stavudine) is not a cure for HIV infection, and that they may continue to acquire illnesses associated with HIV infection, including opportunistic infections. Patients should be advised to remain under the care of a physician when using ZERIT. They should be advised that ZERIT therapy has not been shown to reduce the risk of transmission of HIV to others through sexual contact or blood contamination. Patients should be informed that the long-term effects of ZERIT are unknown at this time.

Patients should be informed that the Centers for Disease Control and Prevention (CDC) recommend that HIV-infected mothers not nurse newborn infants to reduce the risk of postnatal transmission of HIV infection.

Patients should be informed that redistribution or accumulation of body fat may occur in individuals receiving antiretroviral therapy and that the cause and long-term health effects of these conditions are not known at this time.

Patients should be advised of the importance of adherence to any antiretroviral regimen, including those that contain ZERIT.

Drug Interactions (see also CLINICAL PHARMACOLOGY)

Zidovudine competitively inhibits the intracellular phosphorylation of stavudine. Therefore, use of zidovudine in combination with ZERIT should be avoided.

In vitro data indicate that the phosphorylation of stavudine is also inhibited at relevant concentrations by doxorubicin and ribavirin. The clinical significance of these in vitro interactions is unknown; therefore, concomitant use of stavudine with either of these drugs should be undertaken with caution. (See WARNINGS.)

Carcinogenesis, Mutagenesis, Impairment of Fertility

In 2-year carcinogenicity studies in mice and rats, stavudine was noncarcinogenic at doses which produced exposures (AUC) 39 and 168 times, respectively, human exposure at the recommended clinical dose. Benign and malignant liver tumors in mice and rats and malignant urinary bladder tumors in male rats occurred at levels of exposure 250 (mice) and 732 (rats) times human exposure at the recommended clinical dose.

Stavudine was not mutagenic in the Ames, E. coli reverse mutation, or the CHO/HGPRT mammalian cell forward gene mutation assays, with and without metabolic activation. Stavudine produced positive results in the in vitro human lymphocyte clastogenesis and mouse fibroblast assays, and in the in vivo mouse micronucleus test. In the in vitro assays, stavudine elevated the frequency of chromosome aberrations in human lymphocytes (concentrations of 25 to 250 µg/mL, without metabolic activation) and increased the frequency of transformed foci in mouse fibroblast cells (concentrations of 25 to 2500 µg/mL, with and without metabolic activation). In the in vivo micronucleus assay, stavudine was clastogenic in bone marrow cells following oral stavudine administration to mice at dosages of 600 to 2000 mg/kg/day for 3 days.

No evidence of impaired fertility was seen in rats with exposures (based on Cmax) up to 216 times that observed following a clinical dosage of 1 mg/kg/day.

Pregnancy

Pregnancy Category C

Reproduction studies have been performed in rats and rabbits with exposures (based on Cmax) up to 399 and 183 times, respectively, of that seen at a clinical dosage of 1 mg/kg/day and have revealed no evidence of teratogenicity. The incidence in fetuses of a common skeletal variation, unossified or incomplete ossification of sternebra, was increased in rats at 399 times human exposure, while no effect was observed at 216 times human exposure. A slight post-implantation loss was noted at 216 times the human exposure with no effect noted at approximately 135 times the human exposure. An increase in early rat neonatal mortality (birth to 4 days of age) occurred at 399 times the human exposure, while survival of neonates was unaffected at approximately 135 times the human exposure. A study in rats showed that stavudine is transferred to the fetus through the placenta. The concentration in fetal tissue was approximately one-half the concentration in maternal plasma. Animal reproduction studies are not always predictive of human response.

There are no adequate and well-controlled studies of stavudine in pregnant women. Stavudine should be used during pregnancy only if the potential benefit justifies the potential risk.

Fatal lactic acidosis has been reported in pregnant women who received the combination of stavudine and didanosine with other antiretroviral agents. It is unclear if pregnancy augments the risk of lactic acidosis/hepatic steatosis syndrome reported in nonpregnant individuals receiving nucleoside analogues (see WARNINGS: Lactic Acidosis/Severe Hepatomegaly with Steatosis). The combination of stavudine and didanosine should be used with caution during pregnancy and is recommended only if the potential benefit clearly outweighs the potential risk. Healthcare providers caring for HIV-infected pregnant women receiving stavudine should be alert for early diagnosis of lactic acidosis/hepatic steatosis syndrome.

Antiretroviral Pregnancy Registry: To monitor maternal-fetal outcomes of pregnant women exposed to stavudine and other antiretroviral agents, an Antiretroviral Pregnancy Registry has been established. Physicians are encouraged to register patients by calling 1-800-258-4263.

Nursing Mothers

The Centers for Disease Control and Prevention recommend that HIV-infected mothers not breast-feed their infants to avoid risking postnatal transmission of HIV. Studies in lactating rats demonstrated that stavudine is excreted in milk. Although it is not known whether stavudine is excreted in human milk, there exists the potential for adverse effects from stavudine in nursing infants. Because of both the potential for HIV transmission and the potential for serious adverse reactions in nursing infants, mothers should be instructed not to breast-feed if they are receiving ZERIT.

Pediatric Use

Use of stavudine in pediatric patients from birth through adolescence is supported by evidence from adequate and well-controlled studies of stavudine in adults with additional pharmacokinetic and safety data in pediatric patients.

Adverse events and laboratory abnormalities reported to occur in pediatric patients in clinical studies were generally consistent with the safety profile of stavudine in adults. These studies include ACTG 240, where 105 pediatric patients ages 3 months to 6 years received ZERIT 2 mg/kg/day for a median of 6.4 months; a controlled clinical trial where 185 newborns received ZERIT 2 mg/kg/day either alone or in combination with didanosine from birth through 6 weeks of age; and a clinical trial where 8 newborns received ZERIT 2 mg/kg/day in combination with didanosine and nelfinavir from birth through 4 weeks of age.

Stavudine pharmacokinetics have been evaluated in 25 HIV-infected pediatric patients ranging in age from 5 weeks to 15 years and in weight from 2 to 43 kg after IV or oral administration of single doses and twice-daily regimens and in 30 HIV-exposed or -infected newborns ranging in age from birth to 4 weeks after oral administration of twice-daily regimens (see CLINICAL PHARMACOLOGY, Table 3).

Geriatric Use

Clinical studies of ZERIT (stavudine) did not include sufficient numbers of patients aged 65 years and over to determine whether they respond differently than younger patients. Greater sensitivity of some older individuals to the effects of ZERIT cannot be ruled out.

In a monotherapy Expanded Access Program for patients with advanced HIV infection, peripheral neuropathy or peripheral neuropathic symptoms were observed in 15 of 40 (38%) elderly patients receiving 40 mg twice daily and 8 of 51 (16%) elderly patients receiving 20 mg twice daily. Of the approximately 12,000 patients enrolled in the Expanded Access Program, peripheral neuropathy or peripheral neuropathic symptoms developed in 30% of patients receiving 40 mg twice daily and 25% of patients receiving 20 mg twice daily. Elderly patients should be closely monitored for signs and symptoms of peripheral neuropathy.

ZERIT is known to be substantially excreted by the kidney, and the risk of toxic reactions to this drug may be greater in patients with impaired renal function. Because elderly patients are more likely to have decreased renal function, it may be useful to monitor renal function. Dose adjustment is recommended for patients with renal impairment (see DOSAGE AND ADMINISTRATION: Dosage Adjustment).

ADVERSE REACTIONS

Adults

Fatal lactic acidosis has occurred in patients treated with ZERIT in combination with other antiretroviral agents. Patients with suspected lactic acidosis should immediately suspend therapy with ZERIT. Permanent discontinuation of ZERIT should be considered for patients with confirmed lactic acidosis.

ZERIT therapy has rarely been associated with motor weakness, occurring predominantly in the setting of lactic acidosis. If motor weakness develops, ZERIT should be discontinued.

ZERIT therapy has also been associated with peripheral sensory neuropathy, which can be severe, is dose related, and occurs more frequently in patients being treated with other drugs that have been associated with neuropathy (including didanosine), in patients with advanced HIV infection, or in patients who have previously experienced peripheral neuropathy.

Patients should be monitored for the development of neuropathy, which is usually manifested by numbness, tingling, or pain in the feet or hands. Stavudine-related peripheral neuropathy may resolve if therapy is withdrawn promptly. In some cases, symptoms may worsen temporarily following discontinuation of therapy. If symptoms resolve completely, patients may tolerate resumption of treatment at one-half the dose (see DOSAGE AND ADMINISTRATION). If neuropathy recurs after resumption, permanent discontinuation of ZERIT should be considered.

Selected clinical adverse events that occurred in adult patients receiving ZERIT (stavudine) in a controlled monotherapy study (Study AI455-019) are provided in Table 7.

Table 7: Selected Clinical Adverse Events in Study AI455-019a (Monotherapy)
 | Percent (%)
Adverse Events | ZERITb (40 mg twice daily) (n=412) | zidovudine (200 mg 3 times daily) (n=402)
Headache | 54 | 49
Diarrhea | 50 | 44
Peripheral Neurologic Symptoms/Neuropathy | 52 | 39
Rash | 40 | 35
Nausea and Vomiting | 39 | 44
a Any severity, regardless of relationship to study drug.
b Median duration of stavudine therapy = 79 weeks; median duration of zidovudine therapy = 53 weeks.

Pancreatitis was observed in 3 of the 412 adult patients who received ZERIT in a controlled monotherapy study.

Selected clinical adverse events that occurred in antiretroviral-naive adult patients receiving ZERIT from two controlled combination studies are provided in Table 8.

Table 8: Selected Clinical Adverse Eventsa in START 1 and START 2b Studies (Combination Therapy)
 | Percent (%)
 | START 1 |  | START 2b
Adverse Events | ZERIT + lamivudine + indinavir (n=100c) | zidovudine + lamivudine + indinavir (n=102) | ZERIT + didanosine + indinavir (n=102c) | zidovudine + lamivudine + indinavir (n=103)
Nausea | 43 | 63 | 53 | 67
Diarrhea | 34 | 16 | 45 | 39
Headache | 25 | 26 | 46 | 37
Rash | 18 | 13 | 30 | 18
Vomiting | 18 | 33 | 30 | 35
Peripheral NeurologicSymptoms/ Neuropathy | 8 | 7 | 21 | 10
a Any severity, regardless of relationship to study regimen.
b START 2 compared two triple-combination regimens in 205 treatment-naive patients. Patients received either ZERIT (40 mg twice daily) plus didanosine plus indinavir or zidovudine plus lamivudine plus indinavir.
c Duration of stavudine therapy = 48 weeks.

Pancreatitis resulting in death was observed in patients treated with ZERIT plus didanosine in controlled clinical studies and in postmarketing reports.

Selected laboratory abnormalities reported in a controlled monotherapy study (Study AI455‑019) are provided in Table 9.

Table 9: Selected Adult Laboratory Abnormalities in Study AI455-019a,b
 | Percent (%)
Parameter | ZERIT (40 mg twice daily) (n=412) | zidovudine (200 mg 3 times daily) (n=402)
AST (SGOT) (>5.0 x ULN) | 11 | 10
ALT (SGPT) (>5.0 x ULN) | 13 | 11
Amylase (≥1.4 x ULN) | 14 | 13
a Data presented for patients for whom laboratory evaluations were performed.
b Median duration of stavudine therapy = 79 weeks; median duration of zidovudine therapy = 53 weeks.
ULN = upper limit of normal.

Selected laboratory abnormalities reported in two controlled combination studies are provided in Tables 10 and 11.

Table 10: Selected Laboratory Abnormalities in START 1 and START 2 Studies (Grades 3–4)
 | Percent (%)
 | START 1 |  | START 2
Parameter | ZERIT + lamivudine + indinavir (n=100) | zidovudine + lamivudine + indinavir (n=102) | ZERIT + didanosine + indinavir (n=102) | zidovudine + lamivudine + indinavir (n=103)
Bilirubin (>2.6 x ULN) | 7 | 6 | 16 | 8
AST (SGOT) (>5 x ULN) | 5 | 2 | 7 | 7
ALT (SGPT) (>5 x ULN) | 6 | 2 | 8 | 5
GGT (>5 x ULN) | 2 | 2 | 5 | 2
Lipase (>2 x ULN) | 6 | 3 | 5 | 5
Amylase (>2 x ULN) | 4 | <1 | 8 | 2
ULN = upper limit of normal.

Table 11: Selected Laboratory Abnormalities in START 1 and START 2 Studies (All Grades)
 | Percent (%)
 | START 1 |  | START 2
Parameter | ZERIT + lamivudine + indinavir (n=100) | zidovudine + lamivudine + indinavir (n=102) | ZERIT + didanosine + indinavir (n=102) | zidovudine + lamivudine + indinavir (n=103)
Total Bilirubin | 65 | 60 | 68 | 55
AST (SGOT) | 42 | 20 | 53 | 20
ALT (SGPT) | 40 | 20 | 50 | 18
GGT | 15 | 8 | 28 | 12
Lipase | 27 | 12 | 26 | 19
Amylase | 21 | 19 | 31 | 17

Observed During Clinical Practice

The following events have been identified during post-approval use of ZERIT (stavudine). Because they are reported voluntarily from a population of unknown size, estimates of frequency cannot be made. These events have been chosen for inclusion due to their seriousness, frequency of reporting, causal connection to ZERIT, or a combination of these factors.

Body as a Whole—abdominal pain, allergic reaction, chills/fever, and redistribution/accumulation of body fat (see PRECAUTIONS: Fat Redistribution).

Digestive Disorders—anorexia.

Exocrine Gland Disorders—pancreatitis [including fatal cases (see WARNINGS)].

Hematologic Disorders—anemia, leukopenia, thrombocytopenia, and macrocytosis.

Liver—symptomatic hyperlactatemia/lactic acidosis and hepatic steatosis (see WARNINGS), hepatitis and liver failure.

Metabolic Disorders—diabetes mellitus and hyperglycemia.

Musculoskeletal—myalgia.

Nervous System—insomnia, severe motor weakness (most often reported in the setting of lactic acidosis, see WARNINGS).

Use with Didanosine- and Hydroxyurea-Based Regimens

When stavudine is used in combination with other agents with similar toxicities, the incidence of these toxicities may be higher than when stavudine is used alone. Thus, patients treated with ZERIT in combination with didanosine, with or without hydroxyurea, may be at increased risk for pancreatitis and hepatotoxicity, which may be fatal, and severe peripheral neuropathy. The combination of ZERIT and hydroxyurea, with or without didanosine, should be avoided (see WARNINGS and PRECAUTIONS).

Pediatric Patients

Adverse reactions and serious laboratory abnormalities in pediatric patients from birth through adolescence were similar in type and frequency to those seen in adult patients (see PRECAUTIONS: Pediatric Use).

OVERDOSAGE

Experience with adults treated with 12 to 24 times the recommended daily dosage revealed no acute toxicity. Complications of chronic overdosage include peripheral neuropathy and hepatic toxicity. Stavudine can be removed by hemodialysis; the mean ± SD hemodialysis clearance of stavudine is 120 ± 18 mL/min. Whether stavudine is eliminated by peritoneal dialysis has not been studied.

DOSAGE AND ADMINISTRATION

The interval between doses of ZERIT (stavudine) should be 12 hours. ZERIT may be taken with or without food.

Adults: The recommended dose based on body weight is as follows:

40 mg twice daily for patients ≥60 kg.

30 mg twice daily for patients <60 kg.

Pediatrics: The recommended dose for newborns from birth to 13 days old is 0.5 mg/kg/dose given every 12 hours (see CLINICAL PHARMACOLOGY). The recommended dose for pediatric patients at least 14 days old and weighing less than 30 kg is 1 mg/kg/dose, given every 12 hours. Pediatric patients weighing 30 kg or greater should receive the recommended adult dosage.

Dosage Adjustment

Patients should be monitored for the development of peripheral neuropathy, which is usually manifested by numbness, tingling, or pain in the feet or hands. These symptoms may be difficult to detect in young children (see WARNINGS). If these symptoms develop during treatment, stavudine therapy should be interrupted. Symptoms may resolve if therapy is withdrawn promptly. In some cases, symptoms may worsen temporarily following discontinuation of therapy. If symptoms resolve completely, patients may tolerate resumption of treatment at one-half the recommended dose:

20 mg twice daily for patients ≥60 kg.

15 mg twice daily for patients <60 kg.

If peripheral neuropathy recurs after resumption of ZERIT, permanent discontinuation should be considered.

Renal Impairment

ZERIT may be administered to adult patients with impaired renal function with adjustment in dose as shown in Table 12.

Table 12: Recommended Dosage Adjustment for Renal Impairment
Creatinine Clearance (mL/min) | Recommended ZERIT Dose by Patient Weight
Creatinine Clearance (mL/min) | ≥60 kg | <60 kg
>50 | 40 mg every 12 hours | 30 mg every 12 hours
26-50 | 20 mg every 12 hours | 15 mg every 12 hours
10-25 | 20 mg every 24 hours | 15 mg every 24 hours

Since urinary excretion is also a major route of elimination of stavudine in pediatric patients, the clearance of stavudine may be altered in children with renal impairment. Although there are insufficient data to recommend a specific dose adjustment of ZERIT in this patient population, a reduction in the dose and/or an increase in the interval between doses should be considered.

Hemodialysis Patients

The recommended dose is 20 mg every 24 hours (≥60 kg) or 15 mg every 24 hours (<60 kg), administered after the completion of hemodialysis and at the same time of day on non-dialysis days.

Method of Preparation

ZERIT (stavudine) for Oral Solution

Prior to dispensing, the pharmacist must constitute the dry powder with purified water to a concentration of 1 mg stavudine per mL of solution, as follows:

1. Add 202 mL of purified water to the container.
2. Shake container vigorously until the powder dissolves completely. Constitution in this way produces 200 mL (deliverable volume) of 1 mg/mL stavudine solution. The solution may appear slightly hazy.
3. Dispense solution in original container with measuring cup provided. Instruct patient to shake the container vigorously prior to measuring each dose and to store the tightly closed container in a refrigerator, 2° C to 8° C (36° F to 46° F). Discard any unused portion after 30 days.

HOW SUPPLIED

ZERIT® (stavudine) Capsules are supplied by State of Florida DOH Central Pharmacy as follows:

NDC | Strength | Quantity/Form | Color | Source Prod. Code
53808-0656-1 | 20 mg | 30 Capsules in a Blister Pack | light brown | 0003-1965
53808-0657-1 | 30 mg | 30 Capsules in a Blister Pack | light orange & dark orange | 0003-1966
53808-0795-1 | 40 mg | 30 Capsules in a Blister Pack | dark orange | 0003-1967

Storage

ZERIT Capsules should be stored in tightly closed containers at 25° C (77° F). Excursions between 15° C and 30° C (59° F and 86° F) are permitted (see USP Controlled Room Temperature).

ZERIT for Oral Solution should be protected from excessive moisture and stored in tightly closed containers at 25° C (77° F). Excursions between 15° C and 30° C (59° F and 86° F) are permitted (see USP Controlled Room Temperature). After constitution, store tightly closed containers of ZERIT for Oral Solution in a refrigerator, 2° C to 8° C (36° F to 46° F). Discard any unused portion after 30 days.

Bristol-Myers Squibb Company
Princeton, NJ 08543 USA

This Product was Repackaged By:

State of Florida DOH Central Pharmacy
104-2 Hamilton Park Drive
Tallahassee, FL 32304
United States

PATIENT INFORMATION

ZERIT®

(generic name = stavudine, also known as d4T)
ZERIT® (stavudine) Capsules
ZERIT® (stavudine) for Oral Solution

What is ZERIT?

ZERIT (pronounced ZAIR it) is a prescription medicine used in combination with other drugs to treat adults and children who are infected with HIV (the human immunodeficiency virus), the virus that causes AIDS. ZERIT belongs to a class of drugs called nucleoside reverse transcriptase inhibitors (NRTIs). By reducing the growth of HIV, ZERIT helps your body maintain its supply of CD4 cells, which are important for fighting HIV and other infections.

ZERIT (stavudine) will not cure your HIV infection. At present there is no cure for HIV infection. Even while taking ZERIT, you may continue to have HIV-related illnesses, including infections caused by other disease-producing organisms. Continue to see your doctor regularly and report any medical problems that occur.

ZERIT does not prevent a person infected with HIV from passing the virus to other people. To protect others, you must continue to practice safe sex and take precautions to prevent others from coming in contact with your blood and other body fluids.

There is limited information on the long-term use of ZERIT.

Who should not take ZERIT?

Do not take ZERIT if you are allergic to any of its ingredients, including its active ingredient, stavudine, and the inactive ingredients. (See Inactive Ingredients at the end of this leaflet.) Tell your doctor if you think you have had an allergic reaction to any of these ingredients.

How should I take ZERIT? How should I store it?

Your doctor will determine your dose (the amount in each capsule or spoonful) based on your body weight, kidney and liver function, and any side effects that you may have had with other medicines. Take ZERIT exactly as instructed. Try not to miss a dose, but if you do, take it as soon as possible. If it is almost time for the next dose, skip the missed dose and continue your regular dosing schedule. ZERIT may be taken with food or on an empty stomach.

- Capsules: ZERIT capsules are usually taken twice a day (every 12 hours). Store ZERIT capsules in a tightly closed container at room temperature away from heat and out of the reach of children and pets. Do NOT store this medicine in a damp place such as a bathroom medicine cabinet or near the kitchen sink.
- Oral solution (for children): ZERIT for Oral Solution is taken twice a day (every 12 hours). If your child will be taking ZERIT, the doctor should give you written instructions on how to give this medicine. Before measuring each dose, shake the bottle well. Store ZERIT for Oral Solution in a tightly closed container in a refrigerator and throw away any unused portion after 30 days.

If you have a kidney problem:

If your kidneys are not working properly, your doctor may monitor your kidney function while you take ZERIT. Also, your dosage of ZERIT may be adjusted.

What should I do if someone takes an overdosage of ZERIT?

If you suspect that you or someone else has taken an overdose of ZERIT, get medical help right away. Contact a doctor or a poison control center.

What important information should I know about taking ZERIT with other medicines?

- Do not take zidovudine (AZT) while taking ZERIT, because AZT may interfere with the actions of ZERIT. Products containing AZT include Combivir®, Retrovir®, and Trizivir®.
- If you are taking ribavirin or interferon, your doctor may need to monitor your therapy more closely or may consider a change in your therapy.

Tell your doctor or pharmacist about any other medicine, vitamin, supplement, or herbal preparation you are taking.

What about pregnancy and nursing (breast-feeding)?

- It is not known if ZERIT can harm a human fetus. Pregnant women have experienced serious side effects when taking stavudine (the active ingredient in ZERIT) in combination with didanosine and other HIV medicines. ZERIT should be used during pregnancy only after discussion with your doctor. Tell your doctor if you become pregnant or plan to become pregnant while taking ZERIT.
- Because studies have shown ZERIT is in the breast milk of animals receiving the drug, it may be present in human breast milk. The Centers for Disease Control and Prevention (CDC) recommends that HIV-infected mothers not breast-feed to reduce the risk of passing HIV infection to their babies and the potential for serious adverse reactions in nursing infants. Therefore, do not nurse a baby while taking ZERIT.

What are the possible side effects of ZERIT?

- Lactic acidosis, severe increase of lactic acid in the blood, severe liver enlargement, including inflammation (pain and swelling) of the liver, and liver failure, which can cause death, have been reported among patients taking ZERIT. Symptoms of lactic acidosis may include:
  - nausea, vomiting, or unusual or unexpected stomach discomfort;
  - feeling very weak and tired;
  - shortness of breath;
  - weakness in arms and legs.
  If you notice these symptoms or if your medical condition has suddenly changed, stop taking ZERIT and call your doctor right away. Lactic acidosis is a medical emergency that must be treated in a hospital. Women (including pregnant women), overweight patients, and those who have had lengthy treatment with nucleoside medicines are more likely to develop lactic acidosis. Your doctor should closely monitor your liver function if you are taking ZERIT and have a history of heavy alcohol use or a liver condition.
- Peripheral neuropathy is a nerve disorder of the hands and feet. If not recognized promptly, this disorder may worsen. Tell your doctor right away if you or a child taking ZERIT has continuing numbness, tingling, burning, or pain in the feet and/or hands. A child may not recognize these symptoms or know to tell you that his or her feet or hands are numb, burning, tingling, or painful. Ask your child's doctor for instructions on how to find out if your child develops peripheral neuropathy.
  Let your doctor know if you or a child taking ZERIT has ever had peripheral neuropathy, because this condition occurs more often in patients who have had it previously. Peripheral neuropathy is also more likely to occur in patients taking drugs that affect the nerves and in patients with advanced HIV disease, but it can occur at any disease stage. If you develop peripheral neuropathy, your doctor may tell you to stop taking ZERIT. In some cases the symptoms worsen for a short time before getting better. Once symptoms of peripheral neuropathy go away completely, ZERIT may be started again at a lower dose.
- Pancreatitis is a dangerous inflammation of the pancreas. It may cause death. Tell your doctor right away if you develop stomach pain, nausea, or vomiting. These can be signs of pancreatitis. Let your doctor know if you have ever had pancreatitis, regularly drink alcoholic beverages, or have gallstones. Pancreatitis occurs more often in patients with these conditions. It is also more likely in people with advanced HIV disease, but can occur at any disease stage. The combination of ZERIT and didanosine may increase your risk for pancreatitis.

People who take ZERIT along with other medicines that may cause similar side effects may have a higher chance of developing these side effects than if they took ZERIT (stavudine) alone.

Other side effects. In addition to peripheral neuropathy, the most frequent side effects observed in studies of adults taking the recommended dose of ZERIT were headache, diarrhea, rash, nausea, and vomiting. Other side effects may include abdominal pain, muscle pain, insomnia, loss of appetite, chills or fever, allergic reactions, blood disorders, and high blood sugar (hyperglycemia or diabetes).

Changes in body fat have been seen in some patients taking antiretroviral therapy. These changes may include increased amount of fat in the upper back and neck (“buffalo hump”), breast, and around the trunk. Loss of fat from the legs, arms, and face may also happen. The cause and long-term health effects of these conditions are not known at this time.

What else should I know about ZERIT?

If you have diabetes mellitus: ZERIT for Oral Solution contains 50 mg of sucrose (sugar) per mL.

Inactive Ingredients:

ZERIT Capsules: microcrystalline cellulose, sodium starch glycolate, lactose (milk sugar), and magnesium stearate in a hard gelatin shell.

ZERIT for Oral Solution: methylparaben, propylparaben, sodium carboxymethylcellulose, sucrose (table sugar), and flavoring agents.

—————————————————————————————————

This medicine was prescribed for your particular condition. Do not use ZERIT for another condition or give it to others. Keep ZERIT and all other medicines out of the reach of children and pets at all times. Do not keep medicine that is out of date or that you no longer need. Dispose of unused ZERIT through community take-back disposal programs when available or by placing it in an unrecognizable closed container in the household trash.

This summary does not include everything there is to know about ZERIT. Medicines are sometimes prescribed for purposes other than those listed in a Patient Information Leaflet. If you have questions or concerns, or want more information about ZERIT, your physician and pharmacist have the complete prescribing information upon which this leaflet was based. You may want to read it and discuss it with your doctor or other healthcare professional. Remember, no written summary can replace careful discussion with your doctor.

Combivir®, Retrovir®, and Trizivir® are registered trademarks of the GlaxoSmithKline group of companies.

Bristol-Myers Squibb Company
Princeton, NJ 08543 USA

This Patient Information Leaflet has been approved by the U.S. Food and Drug Administration.

1187086A7
Rev July 2009

PRINCIPAL DISPLAY PANEL - 20 mg Label

30 Capsules NDC 53808-0656-1

ZERIT®
(stavudine)
Capsules

Rx only

20 mg

PRINCIPAL DISPLAY PANEL - 30 mg Label

30 Capsules NDC 53808-0657-1

ZERIT®
(stavudine)
Capsules

Rx only

30 mg

PRINCIPAL DISPLAY PANEL - 40 mg Label

30 Capsules NDC 53808-0795-1

ZERIT®
(stavudine)
Capsules

Rx only

40 mg